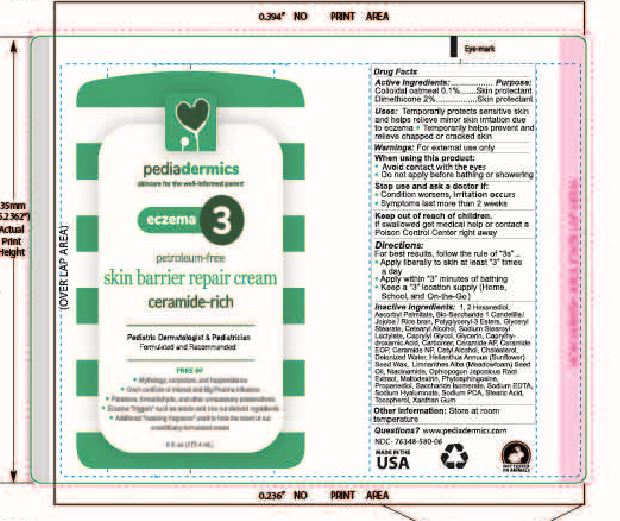 DRUG LABEL: Pediadermics eczema 3
NDC: 76348-580 | Form: CREAM
Manufacturer: Renu Laboratories, LLC
Category: otc | Type: HUMAN OTC DRUG LABEL
Date: 20251202

ACTIVE INGREDIENTS: DIMETHICONE 3.36 g/168 g; OATMEAL 0.168 g/168 g
INACTIVE INGREDIENTS: MEADOWFOAM SEED OIL; CETOSTEARYL ALCOHOL; XANTHAN GUM; CARBOMER HOMOPOLYMER, UNSPECIFIED TYPE; HELIANTHUS ANNUUS SEED WAX; CERAMIDE 1; JOJOBA OIL; RICE BRAN; GLYCERYL MONOSTEARATE; SODIUM STEAROYL LACTYLATE; GLYCERIN; CETYL ALCOHOL; ASCORBYL PALMITATE; CANDELILLA WAX; PROPANEDIOL; NIACINAMIDE; STEARIC ACID; WATER; PHYTOSPHINGOSINE; PALMITIC ACID; BIOSACCHARIDE GUM-1; SODIUM LAUROYL LACTYLATE; CHOLESTEROL; CERAMIDE NP; POLYGLYCERIN-3; CAPRYLYL GLYCOL; SACCHARIDE ISOMERATE; CAPRYLHYDROXAMIC ACID; CERAMIDE AP; EDETATE DISODIUM; HEXANEDIOL; SODIUM HYDROXIDE; HYALURONATE SODIUM; OAT; MALTODEXTRIN; TOCOPHEROL; SODIUM PYRROLIDONE CARBOXYLATE; OPHIOPOGON JAPONICUS ROOT

Pediadermics eczema 3

Active Ingredients

Colloidal oatmeal 0.1%

Dimethicone 2%

Purpose

Skin protectant

Skin protectant

Uses

Temporarily protects sensitive skin and helps relieve minor skin irritation due to eczema. Temporarily helps prevent and relieve chapped or cracked skin.

Warnings

For external use only

When using this product

- Do not get into eyes
- Do not apply before bathing or showering

Stop use and ask a doctor if

Condition worsens

- Symptoms last more than 2 weeks or clear up and occur again within a few days.

Keep out of reach of children.

If swallowed get medical help or contact a Poison Control Center right away.

Directions

For best results, follow the rule of "3"

- Apply liberally to skin at least "3" times a day
- Apply within "3" minutes of bathing
- Keep a "3" location supply (Home, On-the-Go and School) !

Inactive Ingredients

1,2 Hexanediol, Ascorbyl Palmitate, Bio-Saccharide 1, Candelilla / Jojoba / Rice bran, Polyglyceryl-3 Esters, Glyceryl Stearate, Cetearyl Alcohol, Sodium Stearoyl Lactylate, Caprylyl Glycol, Glycerin, Caprylhydroxamic Acid, Carbomer, Ceramide AP, Ceramide EOP, Ceramide NP, Cetyl Alcohol, Cholesterol, Deionized Water, Helianthus Annuus (Sunflower) Seed Wax, Limnanthes Alba (Meadowfoam) Seed Oil, Niacinamide, Ophiopogon Japonicus Root Extract, Maltodextrin, Phytosphingosine, Propanediol, Saccharide Isomerate, Sodium EDTA, Sodium Hyaluronate, Sodium PCA, Stearic Acid, Tocopherol, Xanthan Gum

Other information

Store at room temperature.

Questions?

pediadermics@gmail.com

STATEMENT OF IDENTITY

eczema 3

skin barrier repair cream

PACKAGE LABEL

ECZEMA 3 tube artwork